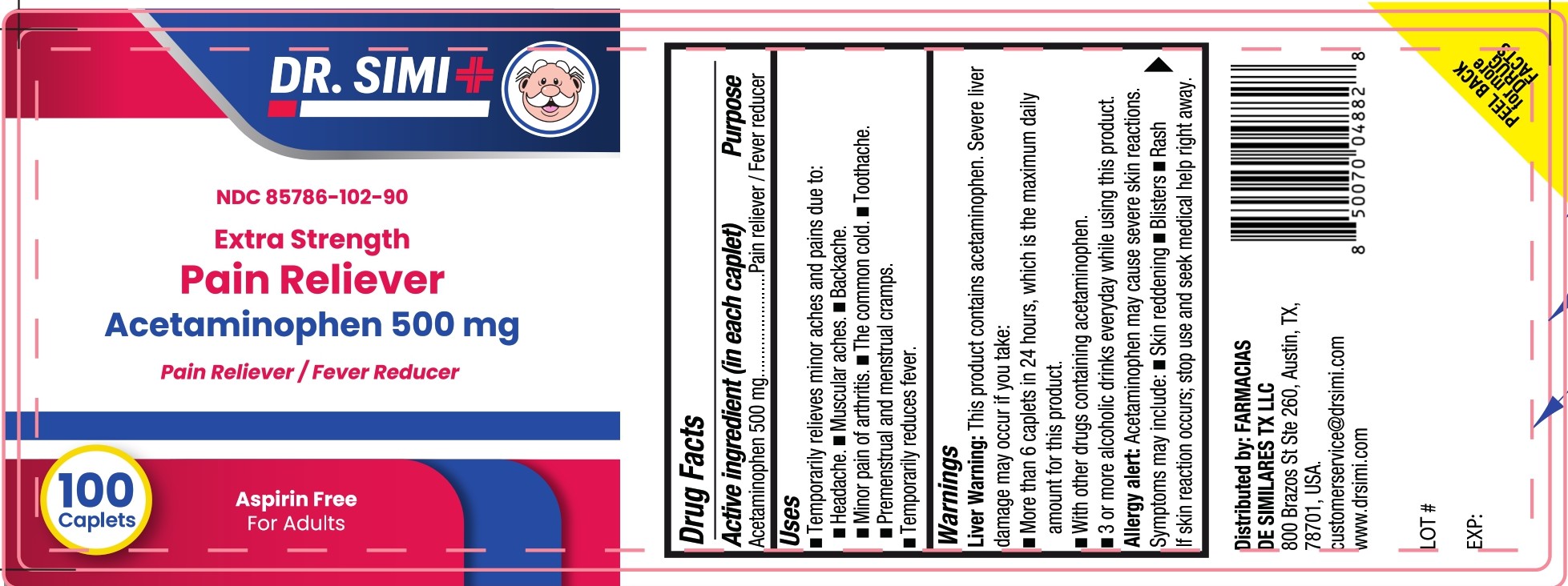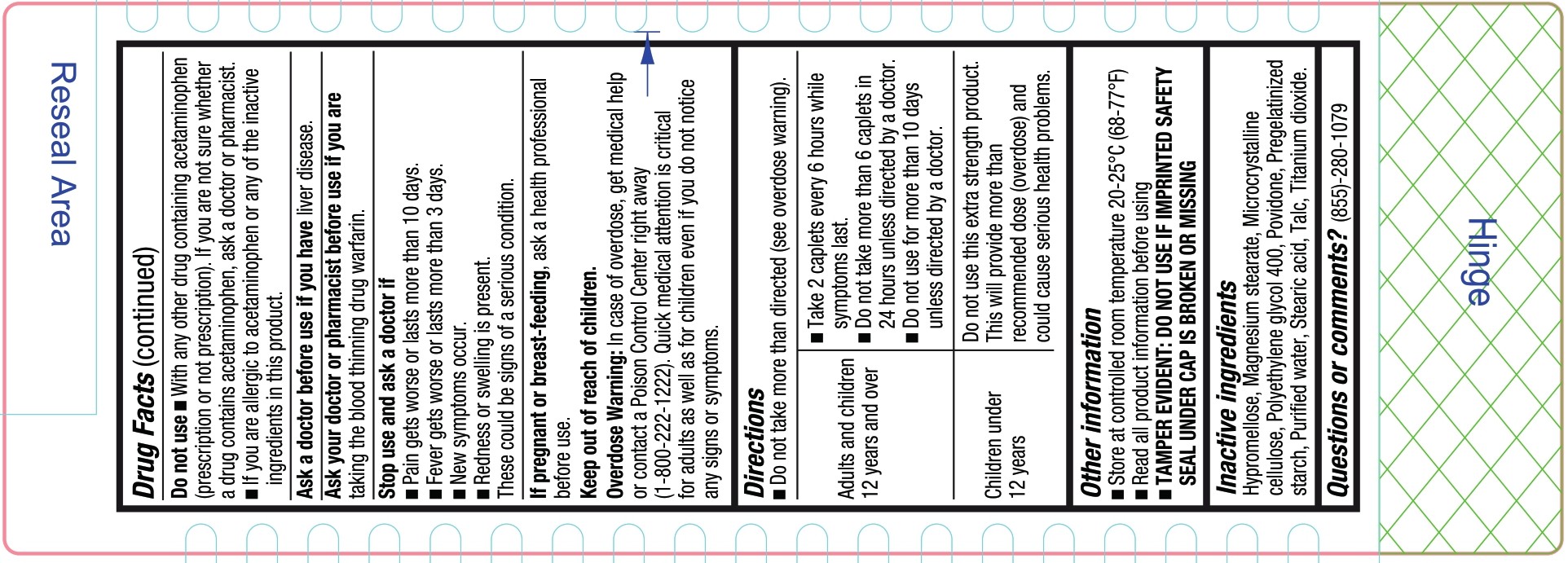 DRUG LABEL: Dr Simi Pain Relief 100
NDC: 85786-102 | Form: TABLET, COATED
Manufacturer: Farmacias De Similares TX LLC
Category: otc | Type: HUMAN OTC DRUG LABEL
Date: 20250813

ACTIVE INGREDIENTS: ACETAMINOPHEN 500 mg/1 1
INACTIVE INGREDIENTS: TALC; STARCH, CORN; TITANIUM DIOXIDE; WATER; STEARIC ACID; POVIDONE K30; MAGNESIUM STEARATE; MICROCRYSTALLINE CELLULOSE; HYPROMELLOSES; POLYETHYLENE GLYCOL 400

Pain Relief 100 Acetaminophen 500

Drug Facts

Active ingredient (in each caplet) | Purpose
Acetaminophen 500 mg | Pain reliever / Fever reducer

Purpose

Active ingredient (in each caplet) | Purpose
Acetaminophen 500 mg | Pain reliever/Fever reducer

Uses

- Temporarily relieves minor aches and pains due to:
- Headache
- Muscular aches
- Backache
- Minor pain of arthritis
- The comon cold
- Toothache
- Premenstrual and menstrual cramps
- Temporarily reduces fever.

Warnings

Warnings

Liver warning: This product contains acetaminophen. Severe liver damage may occur if you take:

- More than 6 caplets in 24 hours, which is the maximum daily amount of this product.
- With other drugs containing acetaminophen.
- 3 or more alcoholic drinks everyday while using this product.

Allergy alert: Acetaminophen may cause severe skin reactions.
Symptoms may include:

- Skin reddening.
- Blisters.
- Rash

If skin reaction occurs; stop use and seek medical help right away.

Do not use

- With any other drug containing acetaminophen (prescription or not prescription). If you are not sure whether a drug contains acetaminophen, ask a doctor or pharmacist.
- If you are allergic to acetaminophen or any of the inactive ingredients in this product

Ask a doctor before use if you have

lliver disease

Ask your doctor or pharmacist before use if you are

- Taking the blood thinning drug warfarin

Stop use and ask a doctor if

- Pain gets worse or lasts more than 10 days.
- Fever gets worse or lasts more than 3 days.
- New symptoms occur.
- Redness or swelling is present.

These could be signs of a serious condition.

If pregnant or breast-feeding

ask a health professional before use

Keep out of reach of children

Overdose warning

In case of overdose, get medical help or contact a Poison Control Center righ away (1-800-222-1222). Quick medical attention is critical for adults as well as for children even if you do not notice any signs or symptoms.

Directions

- Do not take more than directed (see overdose warning).

Directions

Adults and children 12 years of age and over | - Take 2 caplets every 6 hours while symptoms last. - Do not take more than 6 caplets in 24 hours unless directed by a doctor. - Do not use for more than 10 days unless directed by a doctor
Children under 12 years | Do not use this extra strenght product. This will provide more than recommended dose (overdose) and could cause serious health problems.

Other information

- Store at controlled room temperature 20-25°C (68-77°F)
- Read all product information before using
- TAMPER EVIDENT: DO NOT USE IF IMPRINTED SAFETY SEAL UNDER CAP IS BROKEN OR MISSING

Inactive ingredients

Hypromellose, Magnesium stearate, Microcrystalline cellulose, Polyethylene glycol 400, Povidone, Pregelatinized starch, Purified water, Stearic acid, Talc, Titanium dioxide.

Questions or comments?

(855)-280-1079

Distributed by: FARMACIAS DE SIMILARES TX LLC
800 Brazos St Ste 260, Austin, TX, 78701, USA.
customerservice@drsimi.com
www.drsimi.com
LOT #

EXP:

PEEL BACK for more DRUG FACTS

Principal Display Panel

NDC 85786-102-90

Extra Strenght

Pain Reliever

Acetaminophen 500 mg

Pain Reliever/Fever Reducer

100 Caplets

Aspirin Free

For Aduls